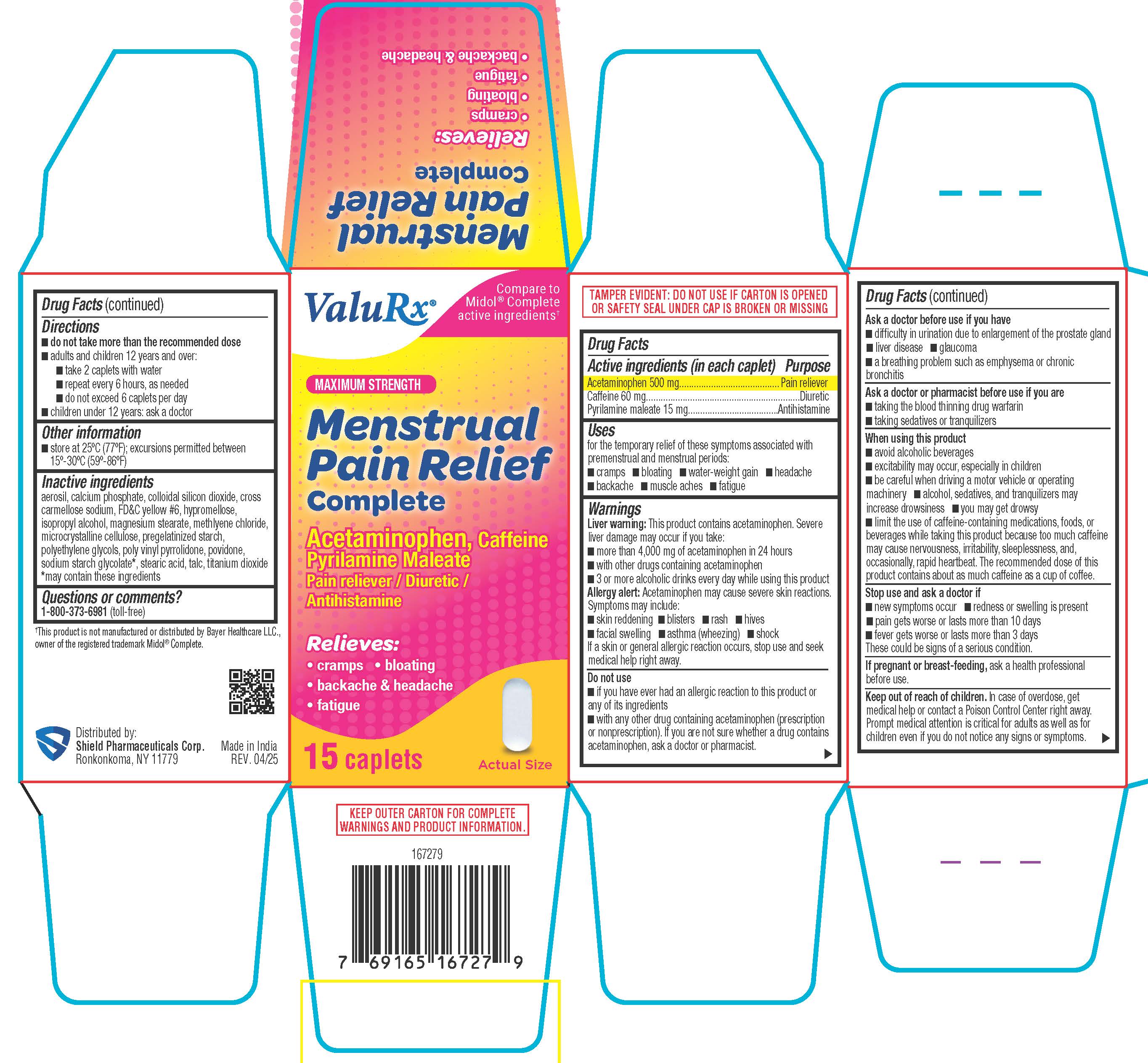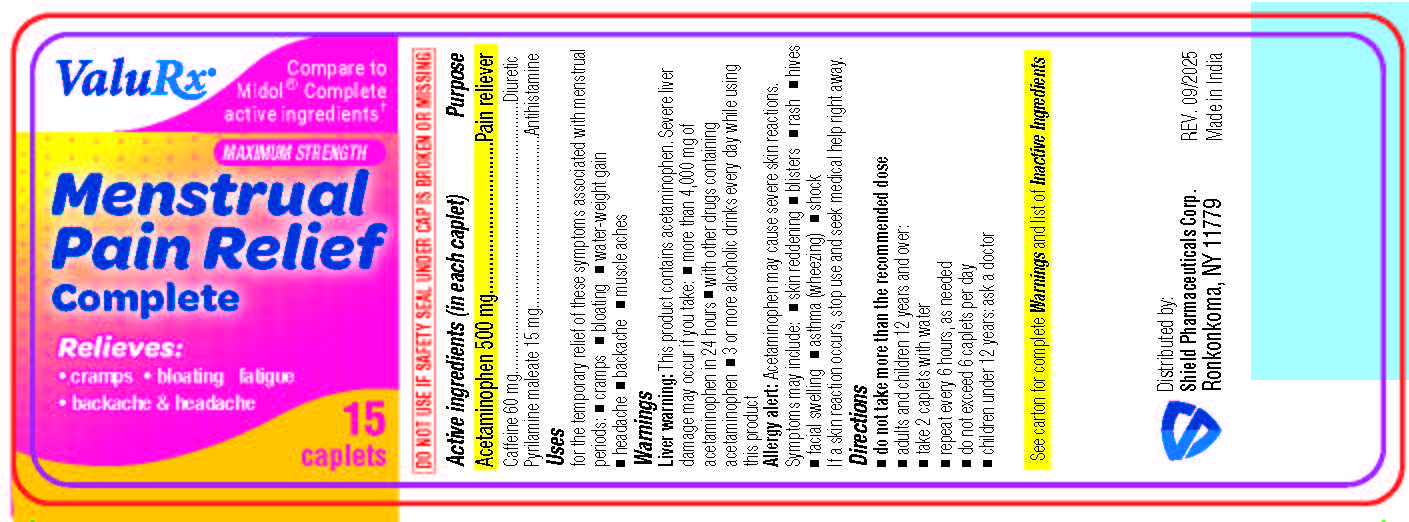 DRUG LABEL: Menstrual Pain Relief Complete
NDC: 83059-0105 | Form: TABLET, FILM COATED
Manufacturer: Shield Pharmaceuticals Corp
Category: otc | Type: HUMAN OTC DRUG LABEL
Date: 20251209

ACTIVE INGREDIENTS: ACETAMINOPHEN 500 mg/1 1; CAFFEINE 60 mg/1 1; PYRILAMINE MALEATE 15 mg/1 1
INACTIVE INGREDIENTS: CALCIUM PHOSPHATE; CROSCARMELLOSE SODIUM; FD&C YELLOW NO. 6; HYPROMELLOSES; ISOPROPYL ALCOHOL; MAGNESIUM STEARATE; METHYLENE CHLORIDE; MICROCRYSTALLINE CELLULOSE; STARCH, CORN; PYRROLIDONE; SODIUM STARCH GLYCOLATE TYPE A; POVIDONE; STEARIC ACID; TALC; TITANIUM DIOXIDE; POLYETHYLENE GLYCOL 400; SILICON DIOXIDE

Menstrual Pain Relief Complete

Drug Facts

Active ingredient (in each liquid-filled capsule)

Acetaminophen 500 mg
Caffeine 60 mg
Pyrilamine maleate 15 mg

Purpose

Pain reliever
Diuretic
Antihistamine

Uses

for the temporary relief of these symptoms associated with menstrual periods:

- cramps
- bloating
- water
- weight gain
- headache
- backache
- muscle aches
- fatigue

Warnings

Liver warning:This product contains acetaminophen. Severe liver damage may occur if you take:

- more than 4,000 mg of acetaminophen in 24 hours
- with other drugs containing acetaminophen
- 3 or more alcoholic drinks every day while using this product

Allergy alert:Acetaminophen may cause severe skin reactions. Symptoms may include:

- skin reddening
- blisters
- rash
- hives
- facial swelling
- asthma (wheezing)
- shock

If a skin reaction occurs, stop use and seek medical help right away.

Do not use

- if you have ever had an allergic reaction to this product or any of its ingredients
- with any other drug containing acetaminophen (prescription or nonprescription). If you are not sure whether a drug contains acetaminophen, ask a doctor or pharmacist.

Ask a doctor before use if you have

- difficulty in urination due to enlargement of the prostate gland
- liver disease _ glaucoma
- a breathing problem such as emphysema or chronic

Ask a doctor or pharmacist before use if youare

- taking the blood thinning drug warfarin
- taking sedatives or tranquilizers

When using this product

- avoid alcoholic beverages
- excitability may occur, especially in children
- be careful when driving a motor vehicle or operating machiner
- alcohol, sedatives, and tranquilizers may increase drowsiness
- you may get drowsy
- limit the use of caffeine-containing medications, foods, or beverages while taking this product because too much caffeine may cause nervousness, irritability, sleeplessness, and, occasionally, rapid heartbeat. The recommended dose of this product contains about as much caffeine as a cup of coffee.

Stop use and ask a doctor if

- new symptoms occur _ redness or swelling is present
- pain gets worse or lasts more than 10 days
- fever gets worse or lasts more than 3 days

These could be signs of a serious condition.

PREGNANCY OR BREAST FEEDING

If pregnant or breast-feeding,ask a health professional before use.

Keep out of reach of children. In case of overdose, get medical help or contact a Poison Control Center right away.
Prompt medical attention is critical for adults as well as for children even if you do not notice any signs or symptoms.

Directions

adults and children 12 years and over:

- do not take more than the recommended dose
- adults and children 12 years and over: take 2 caplets with water
- repeat every 6 hours, as needed
- do not exceed 6 caplets per day
- children under 12 years: ask a doctor

Other information

- store at 25ºC (77ºF); excursions permitted between 15º-30ºC (59º-86ºF)

Inactive ingredients

aerosil, calcium phosphate, colloidal silicon dioxide, cross carmellose sodium, FD&C yellow #6, hypromellose, isopropyl alcohol, magnesium stearate, methlyene chloride, microcrystalline cellulose, pregelatinized starch, polyethylene glycols, poly vinyl pyrrolidone, povidone, sodium starch glycolate*, stearic acid, talc, titanium dioxide
*may contain these ingredients

Distributed by:
Shield Pharmaceuticals Corp.
Ronkonkoma, NY 11779

Questions or comments?

1-800-373-6981 (toll-free)

PRINCIPAL DISPLAY PANEL

Menstrual Pain Relief Complete

Acetaminophen/Caffeine/Pyrilamine maleate

Pain reliever/Diuretic/Antihistamine

Label

Carton